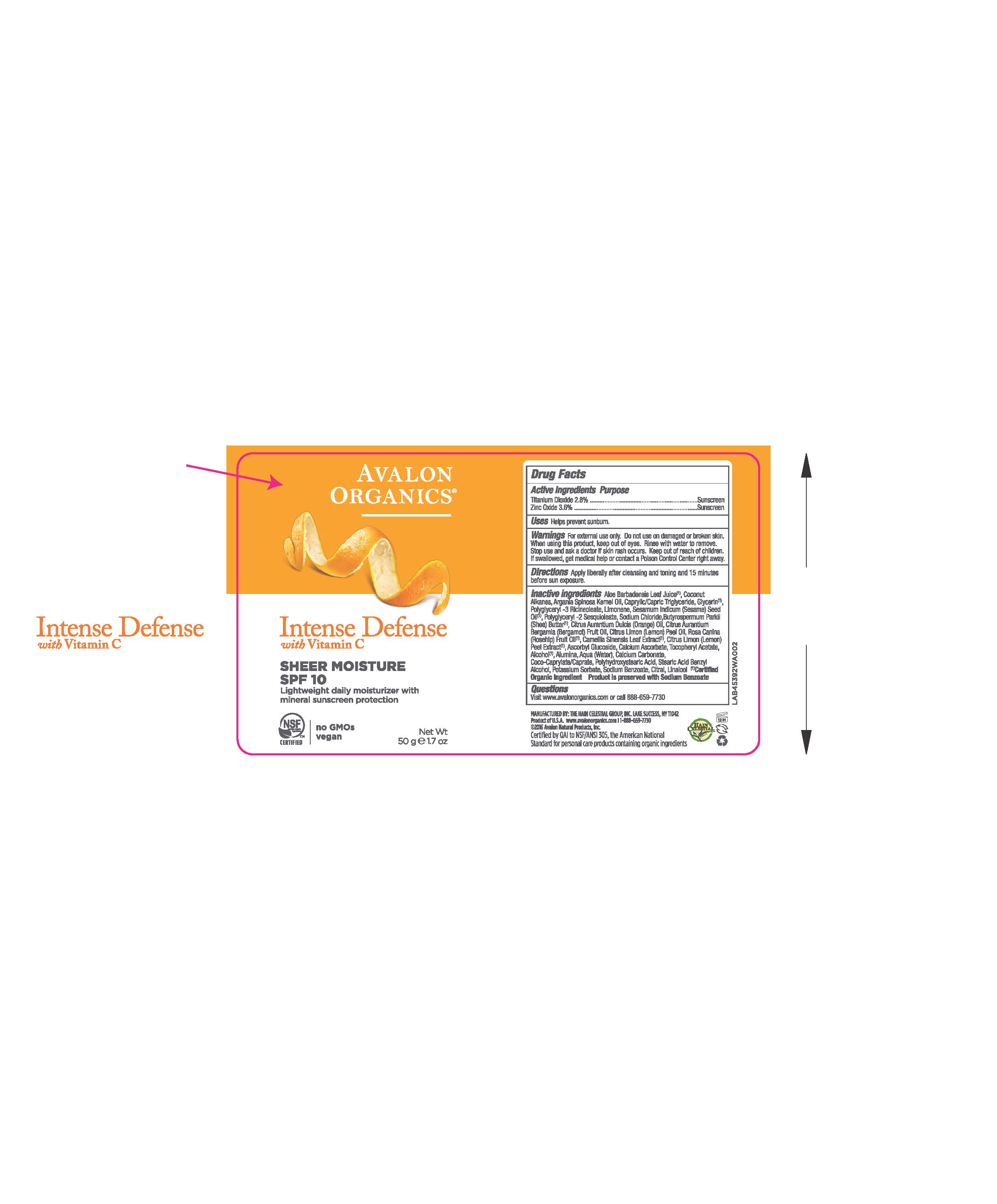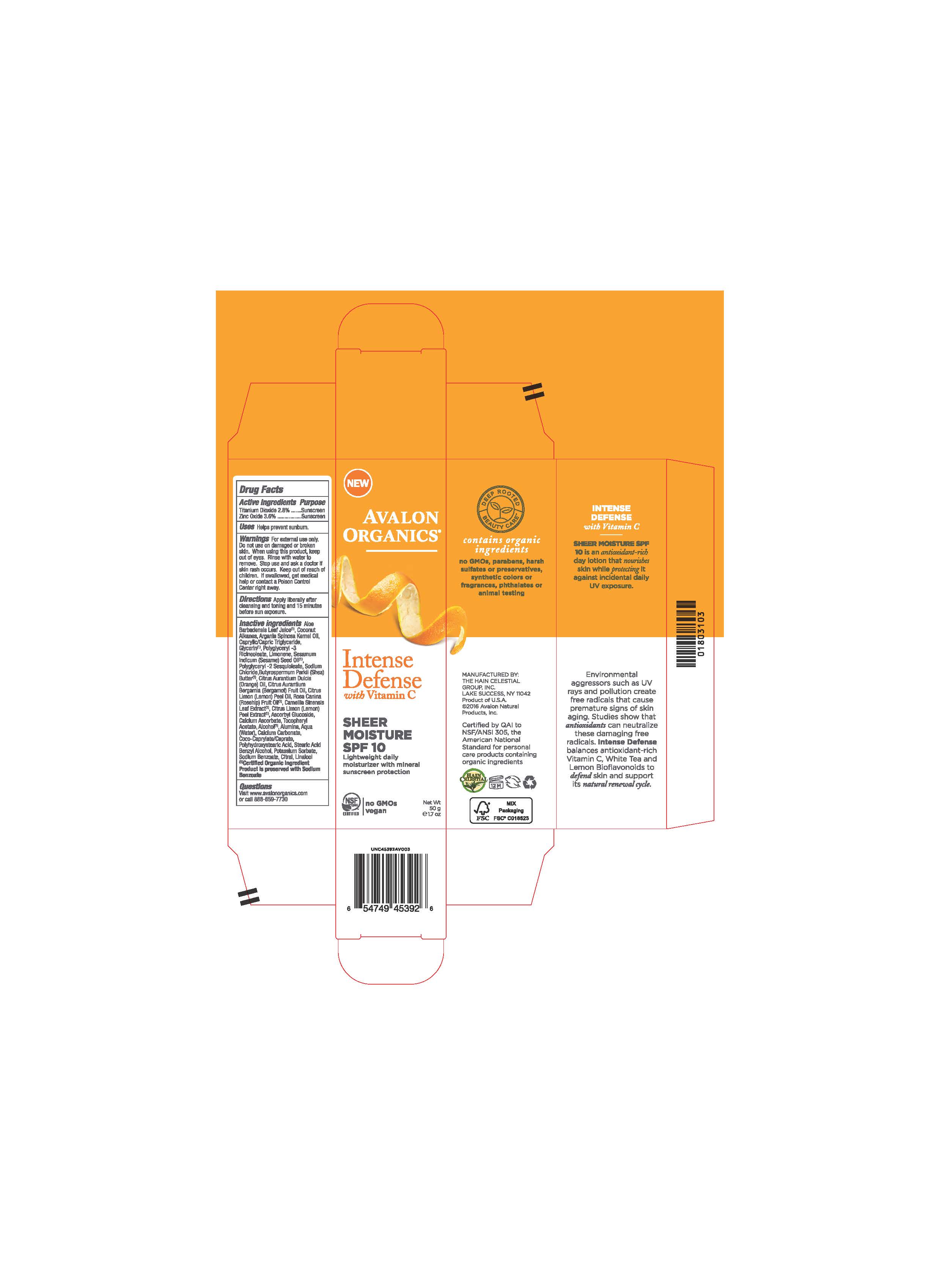 DRUG LABEL: AV453902 Avalon Organics Intense Defense Sheer Moisture SPF10
NDC: 61995-1392 | Form: CREAM
Manufacturer: The Hain Celestial Group, Inc.
Category: otc | Type: HUMAN OTC DRUG LABEL
Date: 20210205

ACTIVE INGREDIENTS: TITANIUM DIOXIDE 2.8 g/100 g; ZINC OXIDE 3.6 g/100 g
INACTIVE INGREDIENTS: LEMON OIL; ROSA CANINA FRUIT OIL; GREEN TEA LEAF; LEMON; ASCORBYL GLUCOSIDE; CALCIUM CARBONATE; POTASSIUM SORBATE; CITRAL; LINALOOL, (+/-)-; BERGAMOT OIL; SODIUM BENZOATE; ORANGE OIL; CALCIUM ASCORBATE; ALCOHOL; BENZYL ALCOHOL; ALOE VERA LEAF; COCONUT ALKANES; GLYCERIN; POLYGLYCERYL-3 RICINOLEATE; WATER; SHEA BUTTER; ALUMINUM OXIDE; COCO-CAPRYLATE/CAPRATE; SODIUM CHLORIDE; STEARIC ACID; POLYHYDROXYSTEARIC ACID (2300 MW); MEDIUM-CHAIN TRIGLYCERIDES; .ALPHA.-TOCOPHEROL ACETATE; LIMONENE, (+)-; SESAME OIL; POLYGLYCERYL-2 SESQUIISOSTEARATE; ARGAN OIL

AV453902 Avalon Organics Intense Defense Sheer Moisture SPF10

Active Ingredient

Zinc Oxide 3.6%

Titanium Dioxide 2.8%

DOSAGE AND ADMINISTRATION

Apply liberally after cleansing and toning and 15 minutes before sun exposure.

PURPOSE

Sunscreen

WARNINGS

For external use only. Do not use on damaged or broken skin. When using this product keep out of eyes. Rinse with water to remove. Stop use and ask a doctor if skin rash occurs.

Keep out of reach of children. If swallowed get medical help or contact Poison Control Center right away.

INACTIVE INGREDIENT

Aloe Barbadensis Leaf Juice(1),Coconut Alkanes, Argania Spinosa Kernel Oil (1), Caprylic Capric Triglyceride, Glycerin, Polyglyceryl-3 Ricinoleate, Limonene, Sesamum Indicum (Sesame) Seed Oil, Polyglyceryl-2 Sesquioleate, Sodium Chloride, Butyrospermum Parkii (Shea) Butter, Citrus Aurantium Dulcis (Orange) Peel Oil, Citrus Aurantium Bergamia (Bergamot) Fruit Oil, Citrus Limon (Lemon) Peel Oil, Rosa Canina (Rosehip) Fruit Oil (1), Camellia Sinensis Leaf Extract (1), Citrus Limon (Lemon) Peel Extract (1), Polyhydroxystearic Acid,Tocopheryl Acetate, Ascorbyl Glucoside, Alumina, Water,Calcium Ascorbate, Calcium Carbonate, Coco-Caprylate/Caprate, Sodium Chloride, Stearic Acid, Alcohol (1), Benzyl Alcohol, Potassium Sorbate, Sodium Benzoate, Citral, Linalool.

(1) Certified Organicf Ingredient

INDICATIONS AND USAGE

Helps prevents sunburns.

QUESTIONS

Visit www.avalonorganics.com or call 888-659-7730